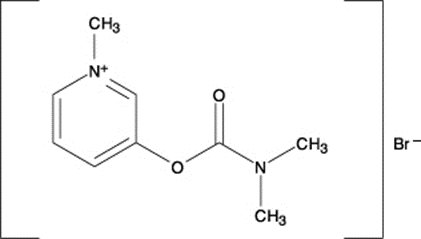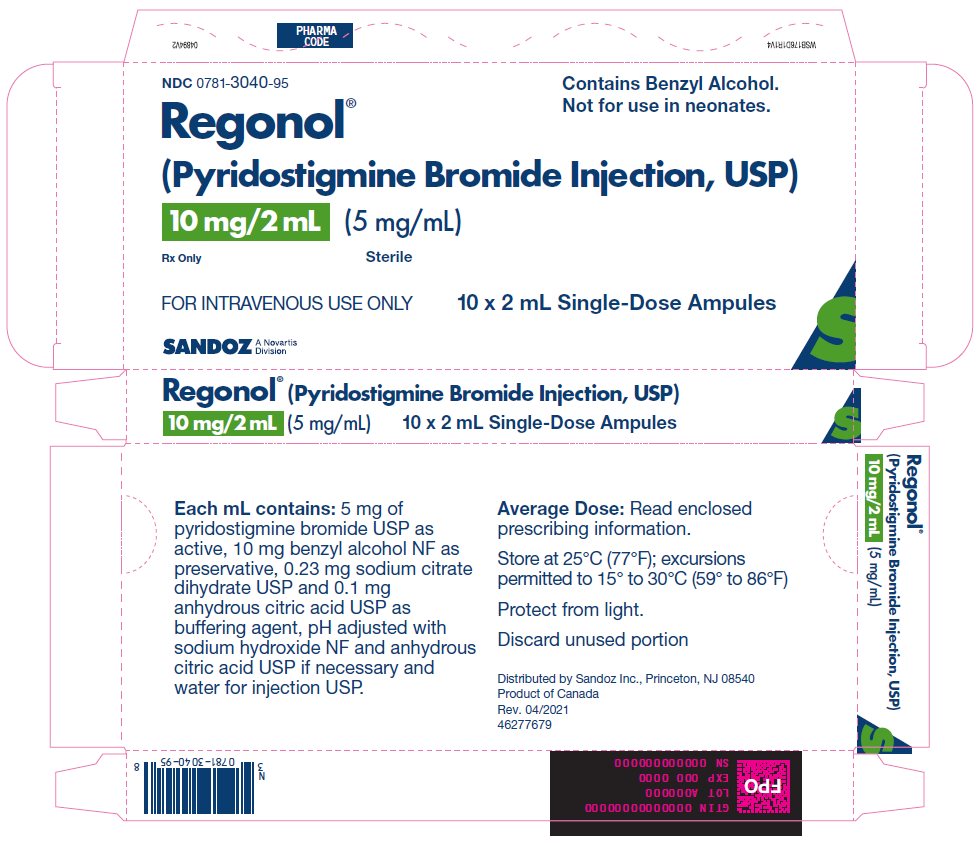 DRUG LABEL: Regonol
NDC: 0781-3040 | Form: INJECTION, SOLUTION
Manufacturer: Sandoz Inc
Category: prescription | Type: HUMAN PRESCRIPTION DRUG LABEL
Date: 20221013

ACTIVE INGREDIENTS: PYRIDOSTIGMINE BROMIDE 5 mg/1 mL
INACTIVE INGREDIENTS: BENZYL ALCOHOL; CITRIC ACID MONOHYDRATE; SODIUM CITRATE, UNSPECIFIED FORM; SODIUM HYDROXIDE; WATER

Regonol® (Pyridostigmine Bromide Injection, USP)

Rx Only

CONTAINS BENZYL ALCOHOL

THIS DRUG SHOULD BE ADMINISTERED BY ADEQUATELY TRAINED INDIVIDUALS FAMILIAR WITH ITS ACTIONS, CHARACTERISTICS, AND HAZARDS.

DESCRIPTION

REGONOL® (pyridostigmine bromide injection, USP) is an active cholinesterase inhibitor chemically designated as 3-hydroxy-1-methylpyridinium bromide dimethyl-carbamate.

Its structural formula is:

REGONOL® is supplied as a sterile, isotonic, nonpyrogenic solution for injection. Each mL contains 5 mg of pyridostigmine bromide USP as active, 10 mg BENZYL ALCOHOL NF as preservative WHICH IS NOT INTENDED FOR USE IN NEWBORNS, 0.23 mg sodium citrate dihydrate USP and 0.1 mg anhydrous citric acid USP as buffering agent, pH adjusted with sodium hydroxide NF and anhydrous citric acid USP if necessary and water for injection USP.

CLINICAL PHARMACOLOGY

REGONOL® (pyridostigmine bromide injection, USP) an analogue of neostigmine, facilitates the transmission of impulses across the myoneural junction by inhibiting the destruction of acetylcholine by cholinesterase. Currently available data indicate that pyridostigmine may have a significantly lower degree and incidence of bradycardia, salivation and gastrointestinal stimulation than does neostigmine. Animal studies using the injectable form of pyridostigmine and human studies using the oral preparation have indicated that pyridostigmine has a longer duration of action than does neostigmine measured under similar circumstances.^1,2 REGONOL® is effective in reversing the neuromuscular blocking effects of nondepolarizing muscle relaxants.

Anticholinesterase agents such as REGONOL® and neostigmine may produce depolarization block when administered at doses above their recommended therapeutic ranges. The therapeutic index of REGONOL® (ratio of reversal dose to blocking dose) is approximately 1:6 (see OVERDOSAGE).^3

The antagonism of neuromuscular blockade by anticholinesterase agents may be influenced by the degree of spontaneous recovery achieved when the reversal agent is administered, by the particular relaxant administered, acid-base balance, body temperature, electrolyte imbalance, concomitant medications such as potent inhalational anesthetics, antibiotics or other drugs which enhance or antagonize the action of nondepolarizing muscle relaxants.^4 The use of peripheral nerve stimulation to determine the degree of neuromuscular blockade is recommended in evaluating the effects of the reversal agents.

Failure of anticholinesterase agents to produce prompt (within 30 minutes) reversal of neuromuscular blockade may occur in the presence of extreme debilitation, carcinomatosis, and with concomitant use of certain broad-spectrum antibiotics, or anesthetic agents and other drugs which enhance neuromuscular blockade or cause respiratory depression through their own pharmacologic actions.

As with other anticholinesterase agents, the administration of REGONOL® may be associated with muscarinic and nicotinic side effects, notably bradycardia and excessive bronchial secretions; the use of glycopyrrolate or atropine sulfate simultaneously with or prior to administration of REGONOL® is recommended to counteract these side effects (see DOSAGE AND ADMINISTRATION).^5

Pharmacokinetics

It has been postulated that the clearance of pyridostigmine is almost equally dependent on metabolism and on urinary elimination of the unchanged drug.^6 Other studies in man indicated that approximately 75 percent of the plasma clearance of pyridostigmine is dependent on renal excretion and the remainder on nonrenal mechanisms.^7

INDICATIONS AND USAGE

REGONOL® (pyridostigmine bromide injection, USP) is indicated as a reversal agent or antagonist to the neuromuscular blocking effects of nondepolarizing muscle relaxants.

CONTRAINDICATIONS

Known hypersensitivity to anticholinesterase agents; intestinal and urinary obstructions of mechanical type.

WARNINGS

NOT FOR USE IN NEONATES

REGONOL® (pyridostigmine bromide injection, USP) should be used with particular caution in patients with bronchial asthma or cardiac dysrhythmias. Transient bradycardia may occur and be relieved by atropine sulfate. Atropine sulfate should also be used with caution in patients with cardiac dysrhythmias. When large doses of pyridostigmine bromide are administered, as during reversal of muscle relaxants, prior or simultaneous injection of atropine sulfate or an equipotent dose of glycopyrrolate is advisable. Because of the possibility of hypersensitivity in an occasional patient, atropine and antishock medication should always be readily available.

When used as an antagonist to nondepolarizing muscle relaxants, adequate recovery of voluntary respiration and neuromuscular transmission must be obtained prior to discontinuation of respiratory assistance, and there should be continuous patient observation. Satisfactory recovery may be judged by adequacy of skeletal muscle tone, respiratory measurements, and by observation of the response to peripheral nerve stimulation. A patent airway should be maintained and manual or mechanical ventilation should be continued until complete recovery of normal respiration is assured.

Exposure to excessive amounts of benzyl alcohol has been associated with toxicity (hypotension, metabolic acidosis), particularly in neonates, and an increased incidence of kernicterus, particularly in small preterm infants. There have been rare reports of deaths, primarily in preterm infants, associated with exposure to excessive amounts of benzyl alcohol. The amount of benzyl alcohol from medications is usually considered negligible compared to that received in flush solutions containing benzyl alcohol. Administration of high dosages of medications containing this preservative must take into account the total amount of benzyl alcohol administered. The amount of benzyl alcohol at which toxicity may occur is not known. If the patient requires more than the recommended dosages or other medications containing this preservative, the practitioner must consider the daily metabolic load of benzyl alcohol from these combined sources (see PRECAUTIONS: Pediatric Use).

PRECAUTIONS

THE USE OF A PERIPHERAL NERVE STIMULATOR TO MONITOR RECOVERY OF NEUROMUSCULAR FUNCTION WILL MINIMIZE THE POSSIBILITY OF EXCESS DOSING OR INADEQUATE REVERSAL.

Inadequate reversal of the neuromuscular blockade induced by nondepolarizing (curariform) muscle relaxants is possible. This can be managed by manual or mechanical ventilation until recovery is judged adequate. The administration of additional doses of anticholinesterase reversal agents is not recommended since excessive dosages of such drugs may produce depolarizing block through their own pharmacologic actions.

Pyridostigmine is mainly excreted unchanged by the kidney.^2,7,8 Therefore, lower doses may be required in patients with renal disease, and treatment should be based on titration of drug dosage to effect.^2,7

Drug Interactions

Concomitant administration of REGONOL® (pyridostigmine bromide injection, USP) and 4-aminopyridine has been reported to delay the onset of action of REGONOL®.^9

Antibiotics

Parenteral administration of high doses of certain antibiotics may intensify or produce neuromuscular block through their own pharmacologic actions. The following antibiotics have been associated with various degrees of paralysis: aminoglycosides (such as neomycin, streptomycin, kanamycin, gentamicin, and dihydrostreptomycin); tetracyclines; bacitracin; polymyxin B; colistin; and sodium colistimethate. If these or other newly introduced antibiotics are used in conjunction with nondepolarizing neuromuscular blocking drugs during surgery, unexpected prolongation of neuromuscular block or resistance to its reversal should be considered a possibility.

Other

Experience concerning injection of quinidine during recovery from use of nondepolarizing muscle relaxants suggest that recurrent paralysis may occur. This possibility must be considered when administering anticholinesterase agents to antagonize neuromuscular blockade induced by nondepolarizing muscle relaxants.

Electrolyte imbalance and diseases which lead to electrolyte imbalance, such as adrenal cortical insufficiency, have been shown to alter neuromuscular blockade. Depending on the nature of the imbalance, either enhancement or inhibition may be expected. Magnesium salts, administered for the management of toxemia of pregnancy, may enhance the neuromuscular blockade. The possibility that such circumstances may interfere with the restoration of neuromuscular function should be considered when administering REGONOL®.

Interactions with Laboratory Tests

None known.

Carcinogenesis, Mutagenesis, Impairment of Fertility

Long-term studies in animals have not been performed to evaluate carcinogenic or mutagenic potential or impairment of fertility.

Pregnancy

It is not known whether REGONOL® (pyridostigmine bromide injection, USP) can cause fetal harm when administered to a pregnant woman or can affect reproductive capacity. REGONOL® should be given to a pregnant woman only if the administering clinician decides that the benefits outweigh the risks.

Pediatric Use

Safety and efficacy in pediatric patients have not been established.

Benzyl alcohol, a component of this drug product, has been associated with serious adverse events and death, particularly in pediatric patients. The “gasping syndrome”, (characterized by central nervous system depression, metabolic acidosis, gasping respirations, and high levels of benzyl alcohol and its metabolites found in the blood and urine) has been associated with benzyl alcohol dosages >99 mg/kg/day in neonates and low-birth-weight neonates. Additional symptoms may include gradual neurological deterioration, seizures, intracranial hemorrhage, hematologic abnormalities, skin breakdown, hepatic and renal failure, hypotension, bradycardia, and cardiovascular collapse. Although normal therapeutic doses of this product deliver amounts of benzyl alcohol that are substantially lower than those reported in association with the “gasping syndrome”, the minimum amount of benzyl alcohol at which toxicity may occur is not known. Premature and low-birth-weight infants, as well as patients receiving high dosages, may be more likely to develop toxicity. Practitioners administering this and other medications containing benzyl alcohol should consider the combined daily metabolic load of benzyl alcohol from all sources.

ADVERSE REACTIONS

The side effects of pyridostigmine bromide are most commonly related to overdosage and generally are of two varieties, muscarinic and nicotinic. Among those in the former group are nausea, vomiting, diarrhea, abdominal cramps, increased peristalsis, increased salivation, increased bronchial secretions, miosis, and diaphoresis. Nicotinic side effects are comprised chiefly of muscle cramps, fasciculation, and weakness. Muscarinic side effects can usually be counteracted by atropine. As with any compound containing the bromide radical, a skin rash may be seen in an occasional patient. Such reactions usually subside promptly upon discontinuance of the medication. Thrombophlebitis has been reported subsequent to intravenous administration.

OVERDOSAGE

THE POSSIBILITY OF IATROGENIC OVERDOSAGE CAN BE MINIMIZED BY CAREFULLY MONITORING THE MUSCLE TWITCH RESPONSE TO PERIPHERAL NERVE STIMULATION. Should overdosage occur, ventilation should be supported by artificial means until the adequacy of spontaneous respiration is assured, and cardiac function should be monitored.

Respiratory depression following administration of nondepolarizing neuromuscular blocking agents may be due either wholly or in part to other drugs used during the conduct of general anesthesia, such as narcotics, thiobarbiturates and other central nervous system depressants. A peripheral nerve stimulator may be used to assess the degree of residual neuromuscular blockade and to help differentiate residual neuromuscular blockade from other causes of decreased respiratory reserve.

DOSAGE AND ADMINISTRATION

REGONOL® (pyridostigmine bromide injection, USP) 2 mL single-dose ampule is for intravenous use only. This drug should be administered by or under the supervision of experienced clinicians familiar with the use of agents which reverse or antagonize the effects of neuromuscular blocking agents. Dosage must be individualized in each case. The dosage information which follows is derived from studies based upon units of drug per unit of body weight and is intended to serve as a guide only. Parenteral drug products should be inspected visually for particulate matter and discoloration prior to administration, whenever solution and container permit.

NOTE: CONTAINS BENZYL ALCOHOL (see PRECAUTIONS)

Reversal doses of REGONOL® range from 0.1 to 0.25 mg/kg.^5,10,11,12,13 The onset time to peak effect is dose-dependent; return of twitch height to 90% of control occurs within approximately 6 minutes following administration of a 0.25 mg/kg dose of REGONOL®.^5,12 At lower doses, full recovery usually occurs within 15 minutes in most patients, although others may require a half-hour or more.

When REGONOL® is given intravenously to reverse the action of muscle relaxant drugs, it is recommended that atropine sulfate (0.6 to 1.2 mg) or an equipotent dose of glycopyrrolate be given immediately prior to or simultaneously with the administration of REGONOL®. Side effects, notably excessive secretions and bradycardia are thereby minimized. Please refer to the appropriate prescribing information prior to the use of glycopyrrolate or atropine sulfate.

To obtain maximum clinical benefits of REGONOL® and to minimize the possibility of overdosage, the monitoring of muscle twitch response to peripheral nerve stimulation is advised. REGONOL® should be administered after spontaneous recovery of neuromuscular function has begun.

Satisfactory reversal can be evident by adequate voluntary respiration, respiratory measurements and use of a peripheral nerve stimulator device. It is recommended that the patient be well-ventilated and a patent airway maintained until complete recovery of normal respiration is assured. Once satisfactory reversal has been attained following administration of REGONOL®, recurrence of paralysis is unlikely to occur.

Inadequate reversal of neuromuscular blockade by anticholinesterase drugs is possible with all curariform drugs, and is managed by manual or mechanical ventilation until recovery is judged adequate. The administration of additional doses of anticholinesterase reversal agents is not recommended since excessive dosages of such drugs may produce depolarizing block through their own pharmacological actions.

Use in Pediatrics

The safety and efficacy of REGONOL® (pyridostigmine bromide injection, USP) in pediatric patients have not been established, therefore no dosing recommendations can be made (see PRECAUTIONS).

HOW SUPPLIED

REGONOL® (pyridostigmine bromide injection USP) for injection is available as 2 mL single-dose ampule containing 10 mg pyridostigmine bromide (5 mg/mL) and supplied as:

NDC 0781-3040-95 - box of 10 x 2 mL Single-Dose Ampules

CONTAINS BENZYL ALCOHOL.

Store at 25°C (77°F); excursions permitted to 15°-30°C (59°-86°F) (see USP Controlled Room Temperature). Protect from light.

REFERENCES

1. Baker PR, Calvey TN, Chan K, Macnee CM, Taylor K. Plasma clearance of neostigmine and pyridostigmine in the dog. Br J Pharmacol 1978;63:509-512.
2. Cronnelly R, Stanski DR, Miller RD, Sheiner LB. Pyridostigmine kinetics with and without renal function. Clin Pharmacol & Ther 1980;28:78-81.
3. Katz RL. Pyridostigmine (Mestinon) as an antagonist of d-tubocurarine. Anesthesiology 1967;28:528-534.
4. Miller RD. Antagonism of neuromuscular blockade. Anesthesiology 1967; 44: 318-329.
5. Gyermek L. Clinical studies on the reversal of the neuromuscular blockade produced by pancuronium bromide. 1. The effects of glycopyrrolate and pyridostigmine. Curr Ther Res 1975; 18:20-23.
6. Williams ME, Calvey TN, Chan K. Plasma concentration of pyridostigmine during the antagonism of neuromuscular block. Br J Anesth 1983; 55:27-30.
7. Miller RD. Pharmacodynamics and pharmacokinetics of anticholinesterase. In: Ruegheimer E, Zindler M, eds., Anaesthesiology, Amsterdam, Netherlands: Excerpta Medica 1981: 222-223.
8. Breyer-Pfaff U, Maier U, Brinkmann AM, Schumm F. Pyridostigmine kinetics in healthy subjects and patients with myasthenia gravis. Clin Pharmacol Ther 1985;5:494-501.
9. Miller RD, Booij LH, Agoston S, Crul JF. 4-aminopyridine potentiates neostigmine and pyridostigmine in man. Anesthesiology 1979;50:416-420.
10. Gyermek L. The Glycopyrrolate-Pyridostigmine Combination. Anesthesiology Review 1978;5:19-22.
11. Zsigmond EK. New Safe and Effective Antagonist of Pancuronium Bromide: Pyridostigmine Bromide. A Scientific Exhibit Presented at the American Medical Association Annual Convention in New York City, NY; June 23-27, 1973.
12. Rusin WD. Comparison of Neostigmine and Pyridostigmine as Antagonists of Pancuronium Neuromuscular Blockade. ASA Clinical Papers, 299-300, 1976.
13. Katz R. Pyridostigmine as an Antagonist of d-Tubocurarine. Anesthesiology 1967;3:528-534.
14. Miller RD, Van Nyhuis LS, Eger EI, Vitez TS, Way WL. Comparative Times to Peak Effect and Durations of Action of Neostigmine and Pyridostigmine. Anesthesiology 1974;41:27-33.
15. Fogdall RP, Miller RD. Antagonism of d-Tubocurarine and Pancuronium Induced Neuromuscular Blockades by Pyridostigmine in Man. Anesthesiology 1973;39:504-509.

Rev. April 2021

46277700

Distributed by

Sandoz Inc., Princeton, NJ 08540

Carton

NDC 0781-3040-95

Regonol® Contains Benzyl Alcohol. Not for use in neonates.

(Pyridostigmine Bromide Injection, USP)

10 mg/2 mL (5 mg/mL)

FOR INTRAVENOUS USE ONLY

Rx only

Sterile

10 x 2 mL Single-Dose Ampules

SANDOZ – A Novartis Division